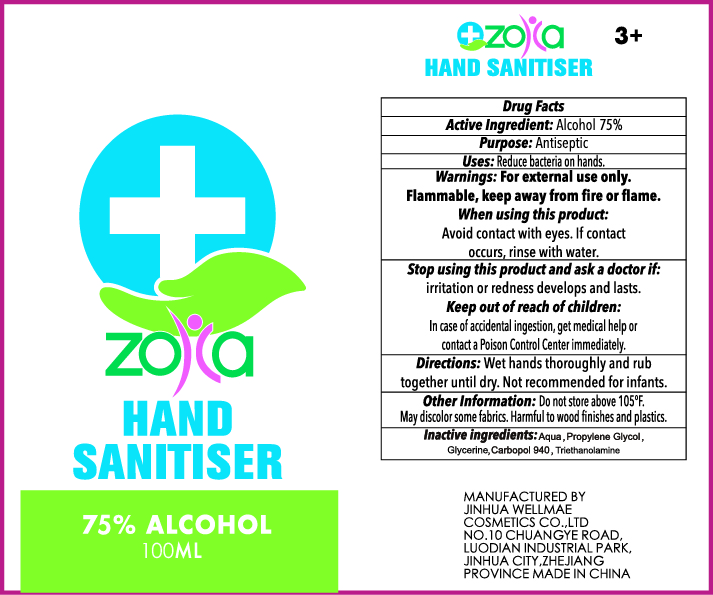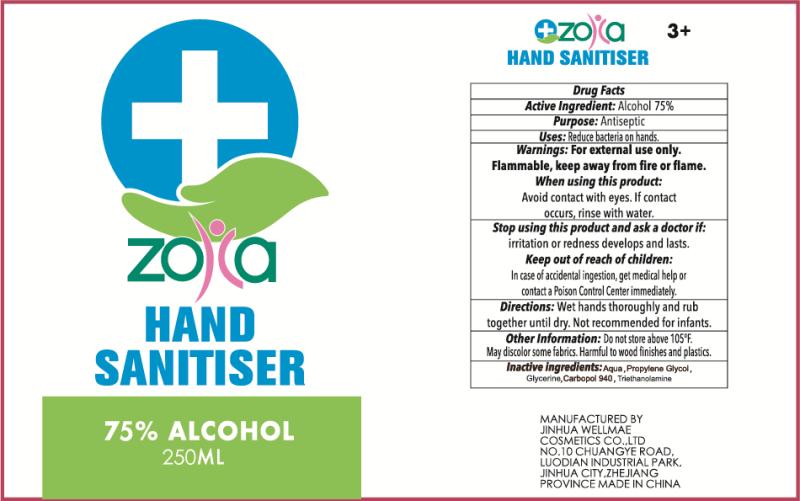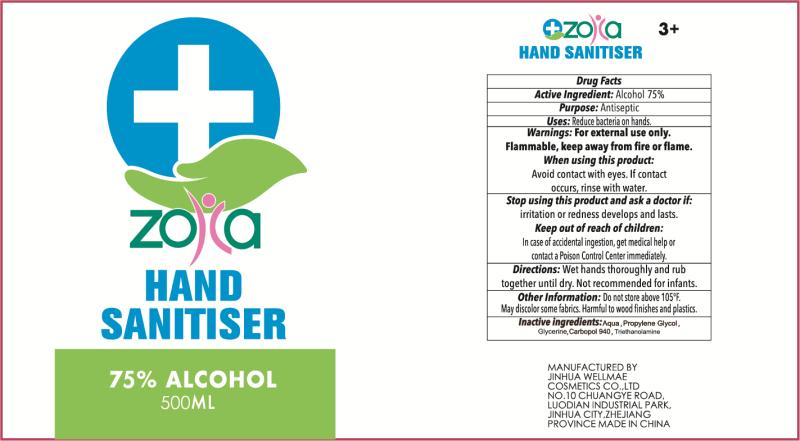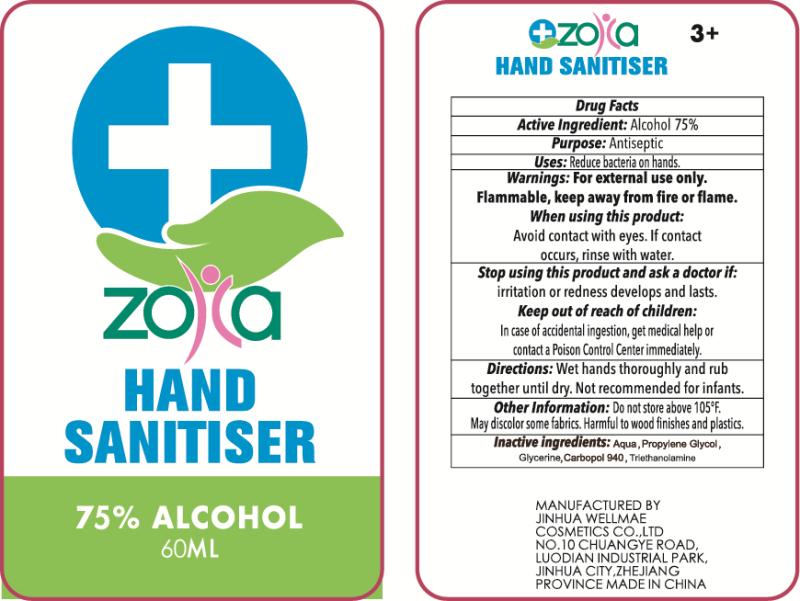 DRUG LABEL: HAND SANITISER
NDC: 75427-003 | Form: GEL
Manufacturer: Jinhua City Wellmae Cosmetics Co., Ltd.
Category: otc | Type: HUMAN OTC DRUG LABEL
Date: 20220119

ACTIVE INGREDIENTS: ALCOHOL 75 mL/100 mL
INACTIVE INGREDIENTS: TROLAMINE; GLYCERIN; PROPYLENE GLYCOL; CARBOMER 940; WATER

75427-003
HAND SANITISER

Active Ingredient(s)

Alcohol 75%

Purpose

Antiseptic

Use

Reduce bacteria on hands.

Warnings

For external use only. Flammable. Keep away from heat or flame

Do not use

Stop using this product and ask a doctor if: irritation or redness develops and lasts.

When using this product:Avoid contact with eyes. If contact occurs, rinse with water.

STOP USE

Stop using this product and ask a doctor if: irritation or redness develops and lasts.

KEEP OUT OF REACH OF CHILDREN

In case of accidental ingestion, cet med al help or contact a Poison Control Center immediatelly

Directions

- Wet hands thoroughly and rub together until dry. Not recommended for infants

Other information

Do not store above105℉

May discolor some fabrics.Harmful to wood finishes and plastics.

Inactive ingredients

Aqua,Propyleone Glycol, Glycerine,Carbopol 940,Triethanolamine